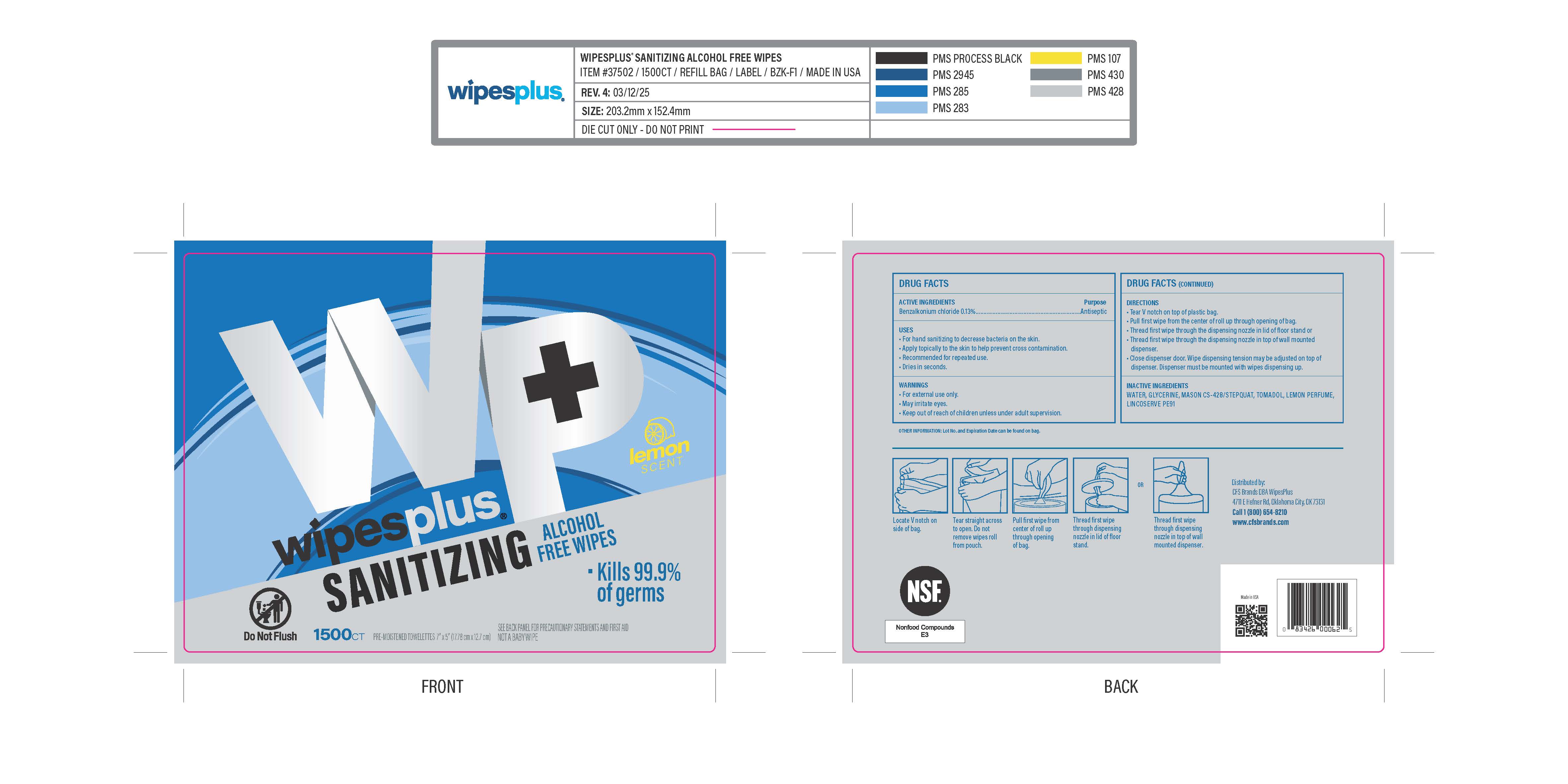 DRUG LABEL: WIPESPLUS HAND SANITIZING ALCOHOL FREE WIPES
NDC: 84376-002 | Form: CLOTH
Manufacturer: CFS Brands
Category: otc | Type: HUMAN OTC DRUG LABEL
Date: 20250430

ACTIVE INGREDIENTS: BENZALKONIUM CHLORIDE 0.78 g/1 1
INACTIVE INGREDIENTS: C9-11 PARETH-8; PHENOXYETHANOL; LEMON; ETHYLHEXYLGLYCERIN; GLYCERIN; WATER

WIPESPLUS HAND SANITIZING ALCOHOL FREE WIPES

Instructions

Rub wipe thoroughly over all surfaces of both hands

allow to dry without wiping

supervise children under 6 years old

not recommended for infants

dispose of wipe in trash, do not flush

Purpose

Purpose antiseptic

BZK

Benzalkonium chloride

DIRECTIONS

-rub wipe thoroughly over all surfaces of both hands

-allow hands to dry without wiping

-supervise children under 6 years old

-not recommended for infants

-dispose of wipe in trash; do not flush

Inactive ingredient

water, glycerin, citrus lemon peel oil, phenoxyethanol, ethylhexylglycerin, C9-11 paretn-9

WARNINGS

external use only

do not take orally

dispose if the wipes have dried out

Do not use in or contact with eyes

Stop using if redness or irritation develops

Keep out of reach of children unless under adult supervision